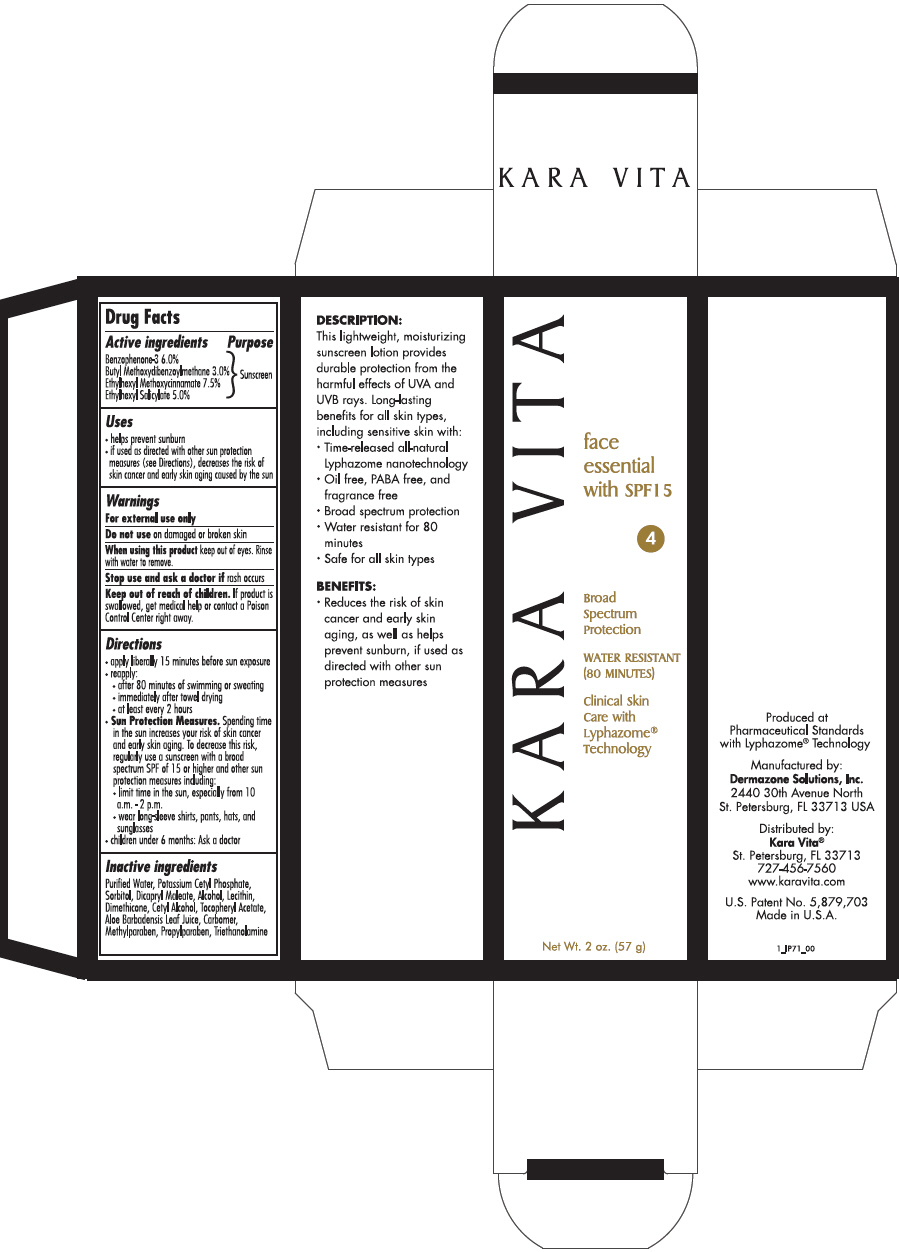 DRUG LABEL: Karavita Face Essential with SPF 15
NDC: 68572-3005 | Form: LOTION
Manufacturer: Kara Vita, Inc.
Category: otc | Type: HUMAN OTC DRUG LABEL
Date: 20181119

ACTIVE INGREDIENTS: OXYBENZONE 60 mg/1 g; AVOBENZONE 30 mg/1 g; OCTINOXATE 75 mg/1 g; OCTISALATE 50 mg/1 g
INACTIVE INGREDIENTS: WATER; POTASSIUM CETYL PHOSPHATE; SORBITOL; ALCOHOL; DIMETHICONE; CETYL ALCOHOL; .ALPHA.-TOCOPHEROL ACETATE; ALOE VERA LEAF; METHYLPARABEN; PROPYLPARABEN; TROLAMINE

Karavita Face Essential with SPF 15

Drug Facts

Active ingredients

Benzophenone-3 6.0%
Butyl Methoxydibenzoylmethane 3.0%
Ethylhexyl Methoxycinnamate 7.5%
Ethylhexyl Salicylate 5.0%

Purpose

Sunscreen

Uses

- helps prevent sunburn
- if used as directed with other sun protection measures (see Directions), decreases the risk of skin cancer and early skin aging caused by the sun

Warnings

For external use only

Do not use on damaged or broken skin

When using this product keep out of eyes. Rinse with water to remove.

Stop use and ask a doctor if rash occurs

Keep out of reach of children. If product is swallowed, get medical help or contact a Poison Control Center right away.

Directions

- apply liberally 15 minutes before sun exposure
- reapply:
  - after 80 minutes of swimming or sweating
  - immediately after towel drying
  - at least every 2 hours
- Sun Protection Measures. Spending time in the sun increases your risk of skin cancer and early skin aging. To decrease this risk, regularly use a sunscreen with a broad spectrum SPF of 15 or higher and other sun protection measures including:
  - limit time in the sun, especially from 10 a.m. - 2 p.m.
  - wear long-sleeve shirts, pants, hats, and sunglasses
- children under 6 months: Ask a doctor

Inactive ingredients

Purified Water, Potassium Cetyl Phosphate, Sorbitol, Dicapryl Maleate, Alcohol, Lecithin, Dimethicone, Cetyl Alcohol, Tocopheryl Acetate, Aloe Barbadensis Leaf Juice, Carbomer, Methylparaben, Propylparaben, Triethanolamine

Manufactured by:
Dermazone Solutions, Inc.
2440 30th Avenue North
St. Petersburg, FL 33713 USA

Distributed by:
Kara Vita®
St. Petersburg, FL 33713

PRINCIPAL DISPLAY PANEL - 57 g Bottle Carton

KARA VITA

face
essential
with SPF15

4

Broad
Spectrum
Protection

WATER RESISTANT
(80 MINUTES)

Clinical Skin
Care with
Lyphazome®
Technology

Net Wt. 2 oz. (57 g)